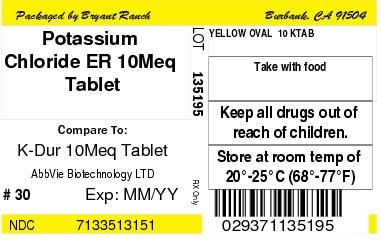 DRUG LABEL: Potassium Chloride
NDC: 71335-1315 | Form: TABLET, FILM COATED, EXTENDED RELEASE
Manufacturer: Bryant Ranch Prepack
Category: prescription | Type: HUMAN PRESCRIPTION DRUG LABEL
Date: 20200917

ACTIVE INGREDIENTS: POTASSIUM CHLORIDE 750 mg/1 1
INACTIVE INGREDIENTS: CASTOR OIL; D&C YELLOW NO. 10; MAGNESIUM STEARATE; PARAFFIN; TITANIUM DIOXIDE; VANILLIN; .ALPHA.-TOCOPHEROL; POLYVINYL ACETATE; SILICON DIOXIDE; ETHYLCELLULOSE, UNSPECIFIED

HIGHLIGHTS OF PRESCRIBING INFORMATION

These highlights do not include all the information needed to use potassium chloride extended-release tablets safely and effectively. See full prescribing information for potassium chloride extended-release tablets.
Potassium chloride extended-release tablets, for oral use
Initial U.S. Approval: 1948

1 INDICATIONS AND USAGE

Potassium chloride extended-release tablets are a potassium salt indicated for the treatment and prophylaxis of hypokalemia with or without metabolic alkalosis in patients for whom dietary management with potassium-rich foods or diuretic dose reduction is insufficient. (1)

2 DOSAGE AND ADMINISTRATION

- Monitor serum potassium and adjust dosages accordingly (2.1)
- If serum potassium concentration is less than 2.5 mEq/L, use intravenous potassium instead of oral supplementation (2.1)
- Take with meals and with a glass of water or other liquid. Swallow tablets whole. (2.1)
- Treatment of hypokalemia: Typical dose range is 40-100 mEq per day in divided doses. Limit doses to 20 mEq per dose. (2.2)
- Prevention of hypokalemia: Typical dose is 20 mEq per day (2.2)

3 DOSAGE FORMS AND STRENGTHS

- 8 mEq (600 mg) oral tablets (3)
- 10 mEq (750 mg) oral tablets (3)
- 20 mEq (1500 mg) oral tablets (3)

4 CONTRAINDICATIONS

- Concomitant use with triamterene and amiloride (4, 7.1)

5 WARNINGS AND PRECAUTIONS

- Gastrointestinal Adverse Reactions: Can produce ulcerative and/or stenotic lesions of the gastrointestinal tract, particularly when in prolonged contact with the gastrointestinal mucosa. Take with meals. (5.1)

6 ADVERSE REACTIONS

Most common adverse reactions are nausea, vomiting, flatulence, abdominal pain/discomfort, and diarrhea (6)

To report SUSPECTED ADVERSE REACTIONS, contact AbbVie Inc. at 1-800-633-9110 or FDA at 1-800-FDA-1088 or www.fda.gov/medwatch.

7 DRUG INTERACTIONS

- Renin-angiotensin-aldosterone system inhibitors: Monitor for hyperkalemia (7.2)
- Nonsteroidal anti-inflammatory drugs: Monitor for hyperkalemia (7.3)

8 USE IN SPECIFIC POPULATIONS

- Cirrhosis: Initiate therapy at the low end of the dosing range (8.6)
- Renal Impairment: Initiate therapy at the low end of the dosing range (8.7)

FULL PRESCRIBING INFORMATION

1 INDICATIONS AND USAGE

Potassium chloride extended-release tablets are indicated for the treatment and prophylaxis of hypokalemia with or without metabolic alkalosis, in patients for whom dietary management with potassium-rich foods or diuretic dose reduction is insufficient.

2 DOSAGE AND ADMINISTRATION

2.1 Monitoring and Administration

If serum potassium concentration is less than 2.5 mEq/L, use intravenous potassium instead of oral supplementation.

Monitoring

Monitor serum potassium and adjust the dose based on serum potassium level. Monitor serum potassium periodically during maintenance therapy to ensure potassium remains in desired range.

The treatment of potassium depletion, particularly in the presence of cardiac disease, renal disease, or acidosis, requires careful attention to acid-base balance, volume status, electrolytes, including magnesium, sodium, chloride, phosphate, and calcium, electrocardiograms, and the clinical status of the patient. Correct volume status, acid-base balance, and electrolyte deficits as appropriate.

Administration

Take potassium chloride extended-release tablets with meals and with a glass of water or other liquid. Do not take on an empty stomach because of its potential for gastric irritation [see Warnings and Precautions (5.1)].

Swallow tablets whole without crushing, chewing or sucking.

2.2 Dosing

Dosage must be adjusted to the individual needs of each patient. Dosages greater than 20 mEq per day should be divided such that no more than 20 mEq is given in a single dose.

Treatment of hypokalemia: Typical dose range is 40-100 mEq per day.

Prevention of hypokalemia: Typical dose is 20 mEq per day.

3 DOSAGE FORMS AND STRENGTHS

- 8 mEq (600 mg): Round, yellow, debossed extended-release tablets with “K-TAB” on one side
- 10 mEq (750 mg): Ovaloid, yellow, debossed extended-release tablets with “10” on one side and “K‑TAB” on the other side
- 10 mEq (750 mg): Ovaloid, yellow, debossed extended-release tablets with the “a” logo on one side and “K‑TAB” on the other side
- 20 mEq (1500 mg): Ovaloid, white, debossed extended-release tablets with “K-TAB” on one side

4 CONTRAINDICATIONS

Potassium chloride is contraindicated in patients on triamterene or amiloride.

5 WARNINGS AND PRECAUTIONS

5.1 Gastrointestinal Adverse Reactions

Solid oral dosage forms of potassium chloride can produce ulcerative and/or stenotic lesions of the gastrointestinal tract, particularly when the drug remains in contact with the gastrointestinal mucosa for a prolonged period of time. Consider the use of liquid potassium in patients with dysphagia, swallowing disorders, or severe gastrointestinal motility disorders.

If severe vomiting, abdominal pain, distention, or gastrointestinal bleeding occurs, discontinue potassium chloride extended-release tablets and consider possibility of ulceration, obstruction or perforation.

Potassium chloride extended-release tablets should not be taken on an empty stomach because of its potential for gastric irritation [see Dosage and Administration (2.1)].

6 ADVERSE REACTIONS

The following adverse reactions have been identified with use of oral potassium salts. Because these reactions are reported voluntarily from a population of uncertain size, it is not always possible to reliably estimate their frequency or establish a causal relationship to drug exposure.

The most common adverse reactions to oral potassium salts are nausea, vomiting, flatulence, abdominal pain/discomfort, and diarrhea.

There have been reports of hyperkalemia and of upper and lower gastrointestinal conditions including obstruction, bleeding, ulceration, perforation [see Warnings and Precautions (5.1) and Overdosage (10)].

Skin rash has been reported rarely.

7 DRUG INTERACTIONS

7.1 Triamterene and Amiloride

Use with triamterene or amiloride can produce severe hyperkalemia. Avoid concomitant use [see Contraindications (4)].

7.2 Renin-Angiotensin-Aldosterone System Inhibitors

Drugs that inhibit the renin-angiotensin-aldosterone system (RAAS) including angiotensin converting enzyme (ACE) inhibitors, angiotensin receptor blockers (ARBs), spironolactone, eplerenone, or aliskiren produce potassium retention by inhibiting aldosterone production. Closely monitor potassium in patients receiving concomitant RAAS therapy.

7.3 Nonsteroidal Anti-Inflammatory Drugs

Nonsteroidal anti-inflammatory drugs (NSAIDs) may produce potassium retention by reducing renal synthesis of prostaglandin E and impairing the renin-angiotensin system. Closely monitor potassium in patients receiving concomitant NSAID therapy.

8 USE IN SPECIFIC POPULATIONS

8.1 Pregnancy

Risk Summary

There are no human data related to use of potassium chloride extended-release tablets during pregnancy, and animal reproduction studies have not been conducted. Potassium supplementation that does not lead to hyperkalemia is not expected to cause fetal harm.

The background risk for major birth defects and miscarriage in the indicated population is unknown. All pregnancies have a background risk of birth defect, loss, or other adverse outcomes. In the U.S. general population, the estimated background risk of major birth defects and miscarriage in clinically recognized pregnancies is 2-4% and 15-20%, respectively.

8.2 Lactation

Risk Summary

The normal potassium ion content of human milk is about 13 mEq per liter. Since potassium from oral supplements such as potassium chloride extended-release tablets becomes part of the body potassium pool, as long as body potassium is not excessive, the contribution of potassium chloride supplementation should have little or no effect on the level in human milk.

8.4 Pediatric Use

Safety and effectiveness of potassium chloride extended-release tablets in children have not been established.

8.5 Geriatric Use

Clinical studies of potassium chloride extended-release tablets did not include sufficient numbers of subjects aged 65 and over to determine whether they respond differently from younger subjects. Other reported clinical experience has not identified differences in responses between the elderly and younger patients. In general, dose selection for an elderly patient should be cautious, usually starting at the low end of the dosing range, reflecting the greater frequency of decreased hepatic, renal or cardiac function, and of concomitant disease or other drug therapy.

This drug is known to be substantially excreted by the kidney, and the risk of toxic reactions to this drug may be greater in patients with impaired renal function. Because elderly patients are more likely to have decreased renal function, care should be taken in dose selection, and it may be useful to monitor renal function.

8.6 Cirrhotics

Doses of potassium in patients with cirrhosis produce a larger increase in potassium levels compared to the response in normal patients. Based on published literature, the baseline corrected serum concentrations of potassium measured over 3 hours after administration in cirrhotic subjects who received an oral potassium load rose to approximately twice that of normal subjects who received the same load. Patients with cirrhosis should usually be started at the low end of the dosing range, and the serum potassium level should be monitored frequently.

8.7 Renal Impairment

Patients with renal impairment have reduced urinary excretion of potassium and are at substantially increased risk of hyperkalemia. Patients with impaired renal function, particularly if the patient is on RAAS inhibitors or NSAIDs, should usually be started at the low end of the dosing range because of the potential for development of hyperkalemia [see Drug Interactions (7.2, 7.3)]. The serum potassium level should be monitored frequently. Renal function should be assessed periodically.

10 OVERDOSAGE

10.1 Symptoms

The administration of oral potassium salts to persons with normal excretory mechanisms for potassium rarely causes serious hyperkalemia. However, if excretory mechanisms are impaired, potentially fatal hyperkalemia can result [see Contraindications (4) and Warnings and Precautions (5.1)].

Hyperkalemia is usually asymptomatic and may be manifested only by an increased serum potassium concentration (6.5-8.0 mEq/L) and characteristic electrocardiographic changes (peaking of T-waves, loss P-waves, depression of S-T segments, and prolongation of the QT intervals). Late manifestations include muscle paralysis and cardiovascular collapse from cardiac arrest (9-12 mEq/L).

10.2 Treatment

Treatment measures for hyperkalemia include the following:

1. Monitor closely for arrhythmias and electrolyte changes.
2. Eliminate foods and medications containing potassium and of any agents with potassium-sparing properties such as potassium-sparing diuretics, ARBs, ACE inhibitors, NSAIDs, certain nutritional supplements, and many others.
3. Administer intravenous calcium gluconate if the patient is at no risk or low risk of developing digitalis toxicity.
4. Administer intravenously 300 to 500 mL/hr of 10% dextrose solution containing 10 to 20 units of crystalline insulin per 1,000 mL.
5. Correct acidosis, if present, with intravenous sodium bicarbonate.
6. Use exchange resins, hemodialysis, or peritoneal dialysis.

In patients who have been stabilized on digitalis, too rapid a lowering of the serum potassium concentration can produce digitalis toxicity.

The extended release feature means that absorption and toxic effects may be delayed for hours. Consider standard measures to remove any unabsorbed drug.

11 DESCRIPTION

Potassium chloride extended-release tablets are a solid oral dosage form of potassium chloride containing 600 mg, 750 mg and 1500 mg of potassium chloride, USP, equivalent to 8 mEq, 10mEq and 20 mEq of potassium, respectively, in a film-coated (not enteric-coated), wax matrix tablet.

The chemical name is potassium chloride, and the structural formula is KCl. Potassium chloride, USP, occurs as a white, granular powder or as colorless crystals. It is odorless and has a saline taste. Its solutions are neutral to litmus. It is freely soluble in water and insoluble in alcohol.

The 8 mEq and 10 mEq tablets also contain castor oil, cellulosic polymers, colloidal silicon dioxide, D&C Yellow No. 10, magnesium stearate, paraffin, polyvinyl acetate, titanium dioxide, vanillin, and vitamin E.

The 20 mEq tablets also contain castor oil, cellulosic polymers, colloidal silicon dioxide, magnesium stearate, paraffin, polyvinyl acetate, titanium dioxide, vanillin, and vitamin E.

12 CLINICAL PHARMACOLOGY

12.1 Mechanism of Action

The potassium ion (K^+) is the principal intracellular cation of most body tissues. Potassium ions participate in a number of essential physiological processes including the maintenance of intracellular tonicity; the transmission of nerve impulse; the contraction of cardiac, skeletal and smooth muscle; and the maintenance of normal renal function.

The intracellular concentration of potassium is approximately 150 to 160 mEq per liter. The normal adult plasma concentration is 3.5 to 5 mEq per liter. An active ion transport system maintains this gradient across the plasma membrane.

Potassium is a normal dietary constituent, and under steady state conditions, the amount of potassium absorbed from the gastrointestinal tract is equal to the amount excreted in the urine. The usual dietary intake of potassium is 50 to 100 mEq per day.

12.2 Pharmacokinetics

Specific Populations

Cirrhotics

Based on published literature, the baseline corrected serum concentrations of potassium measured over 3 hours after administration in cirrhotic subjects who received an oral potassium load rose to approximately twice that of normal subjects who received the same load [see Use in Specific Populations (8.6)].

13 NONCLINICAL TOXICOLOGY

13.1 Carcinogenesis, Mutagenesis, Impairment of Fertility

Carcinogenicity, mutagenicity and fertility studies in animals have not been performed. Potassium is a normal dietary constituent.

16 HOW SUPPLIED/STORAGE AND HANDLING

Product: 71335-1315

NDC: 71335-1315-1 30 TABLET, FILM COATED, EXTENDED RELEASE in a BOTTLE

NDC: 71335-1315-2 60 TABLET, FILM COATED, EXTENDED RELEASE in a BOTTLE

NDC: 71335-1315-3 90 TABLET, FILM COATED, EXTENDED RELEASE in a BOTTLE

NDC: 71335-1315-4 15 TABLET, FILM COATED, EXTENDED RELEASE in a BOTTLE

NDC: 71335-1315-5 180 TABLET, FILM COATED, EXTENDED RELEASE in a BOTTLE

NDC: 71335-1315-6 28 TABLET, FILM COATED, EXTENDED RELEASE in a BOTTLE

NDC: 71335-1315-7 10 TABLET, FILM COATED, EXTENDED RELEASE in a BOTTLE

17 PATIENT COUNSELING INFORMATION

- Inform patients to take each dose with meals and with a full glass of water or other liquid, and to not crush, chew, or suck the tablets.
- Advise patients to seek medical attention if tarry stools or other evidence of gastrointestinal bleeding is noticed.
- Inform patients that the wax tablet is not absorbed and may be excreted intact in the stool. If the patient observes this, it is not an indication of lack of effect.

Manufactured by:
AbbVie LTD
Barceloneta, PR 00617
Distributed by:
Zydus Pharmaceuticals USA Inc.
Pennington, NJ 08534
03-B637 May, 2018